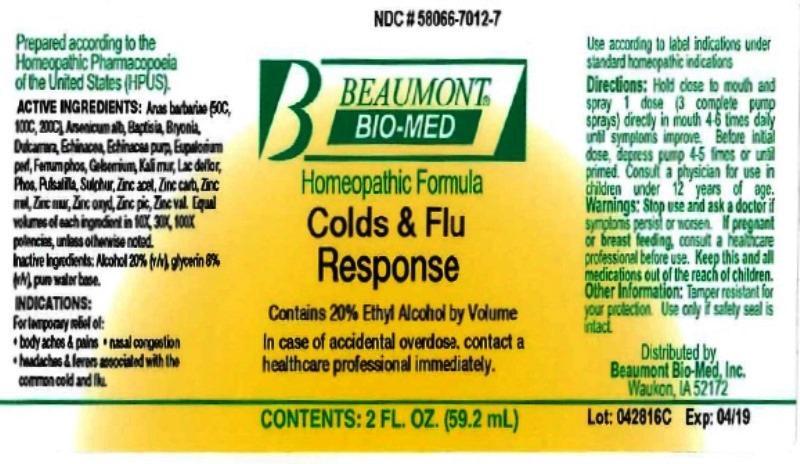 DRUG LABEL: Colds and Flu Response
NDC: 58066-7012 | Form: LIQUID
Manufacturer: Beaumont Bio Med
Category: homeopathic | Type: HUMAN OTC DRUG LABEL
Date: 20160912

ACTIVE INGREDIENTS: CAIRINA MOSCHATA HEART/LIVER AUTOLYSATE 50 [hp_C]/59.2 mL; ARSENIC TRIOXIDE 10 [hp_X]/59.2 mL; BAPTISIA TINCTORIA ROOT 10 [hp_X]/59.2 mL; BRYONIA ALBA ROOT 10 [hp_X]/59.2 mL; SOLANUM DULCAMARA TOP 10 [hp_X]/59.2 mL; ECHINACEA, UNSPECIFIED 10 [hp_X]/59.2 mL; ECHINACEA PURPUREA 10 [hp_X]/59.2 mL; EUPATORIUM PERFOLIATUM FLOWERING TOP 10 [hp_X]/59.2 mL; FERROSOFERRIC PHOSPHATE 10 [hp_X]/59.2 mL; GELSEMIUM SEMPERVIRENS ROOT 10 [hp_X]/59.2 mL; POTASSIUM CHLORIDE 10 [hp_X]/59.2 mL; SKIM MILK 10 [hp_X]/59.2 mL; PHOSPHORUS 10 1/59.2 mL; PULSATILLA VULGARIS 10 [hp_X]/59.2 mL; SULFUR 10 [hp_X]/59.2 mL; ZINC ACETATE ANHYDROUS 10 [hp_X]/59.2 mL; ZINC CARBONATE 10 [hp_X]/59.2 mL; ZINC 10 [hp_X]/59.2 mL; ZINC CHLORIDE 10 [hp_X]/59.2 mL; ZINC OXIDE 10 [hp_X]/59.2 mL; ZINC PICRATE NONAHYDRATE 10 [hp_X]/59.2 mL; ZINC VALERATE DIHYDRATE 10 [hp_X]/59.2 mL
INACTIVE INGREDIENTS: ALCOHOL; GLYCERIN; WATER

Colds and Flu Response

ACTIVE INGREDIENT

HPUS active ingredients: Anas barbariae, hepatis et cordis extractum (50C, 100C, 200C), Arsenicum album, Baptisia tinctoria, Bryonia, Dulcamara, Echinacea, Echinacea purpurea, Eupatorium perfoliatum, Ferrum phosphoricum, Gelsemium sempervirens, Kali muriaticum, Lac defloratum, Phosphorus, Pulsatilla, Sulphur, Zincum aceticum, Zincum carbonicum, Zincum metallicum, Zincum oxydatum, Zincum picricum, Zincum valerianicum. Equal volumes of each ingredient in 10X, 30X, 100X potencies, unless otherwise noted.

INACTIVE INGREDIENT

Inactive Ingredients: Alcohol 20%, (v/v) glycerin 8% (v/v), pure water base.

INDICATIONS AND USAGE

Indications: For temporary relief of: •body aches & pains •nasal congestion •headaches & fevers associated with the common cold and flu.

Use according to label indications under standard homeopathic indications.

DOSAGE AND ADMINISTRATION

Directions: Hold close to mouth and spray 1 dose (3 complete pump sprays) directly in mouth 4-6 times daily until symptoms improve. Before initial dose, depress pump 4-5 times or until primed. Consult a physician for use in children under 12 years of age.

WARNINGS

Warnings: Stop use and ask a doctor if symptoms persist or worsen. If you are pregnant or breast feeding, consult a healthcare professional before use.

KEEP OUT OF REACH OF CHILDREN

- Keep this and all medications out of reach of children.

Other Information: Tamper resistant for your protection. Use only if safety seal is intact. Contains 20% Ethyl Alcohol by Volume. In case of accidental overdose, contact a healthcare professional immediately.

PURPOSE

For temporary relief of:

- body aches & pains
- nasal congestion
- headaches & fevers associated with the common cold and flu